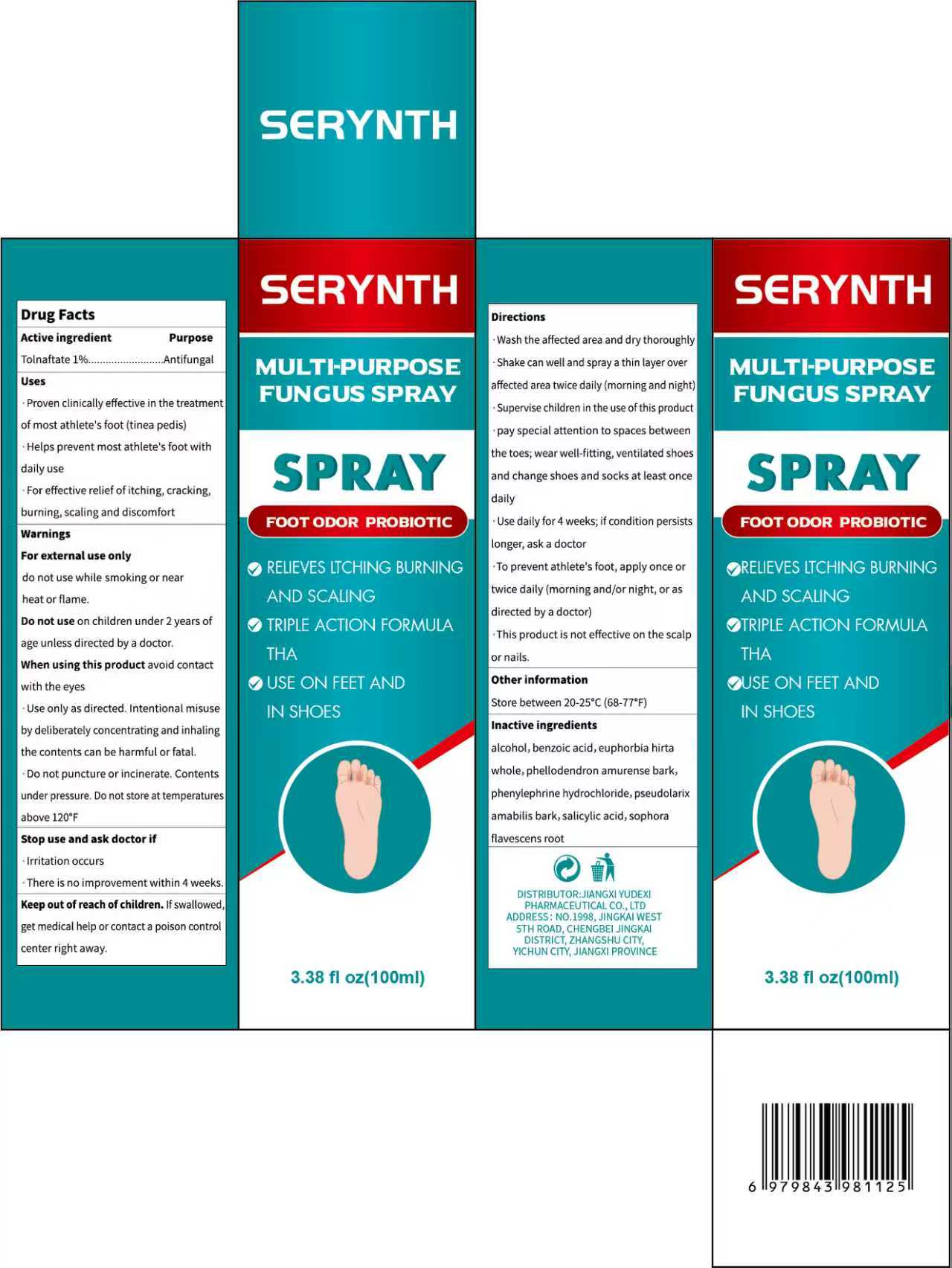 DRUG LABEL: SERYNTH MULTI-PURPOSE FUNCUS
NDC: 85248-133 | Form: SPRAY
Manufacturer: Jiangxi Yudexi Pharmaceutical Co., LTD
Category: otc | Type: HUMAN OTC DRUG LABEL
Date: 20260209

ACTIVE INGREDIENTS: TOLNAFTATE 1 g/100 mL
INACTIVE INGREDIENTS: PSEUDOLARIX AMABILIS BARK; SALICYLIC ACID; SOPHORA FLAVESCENS ROOT; PHENYLEPHRINE HYDROCHLORIDE; PHELLODENDRON AMURENSE BARK; ALCOHOL; BENZOIC ACID; EUPHORBIA HIRTA WHOLE

85248-133

Active Ingredient

Tolnaftate 1%

Purpose

Antifungal

Use

. Proven clinically effective in the treatment
of most athlete's foot (tinea pedis)
· Helps prevent most athlete's foot with daily use
. For effective relief of itching, cracking,burning,scaling and discomfort

Warnings

For external use only do not use while smoking or near heat or flame.

Do not use

on children under 2 years of age unless directed by a doctor.

When Using

this product avoid contact with the eyes
.Use only as directed. Intentional misuse by deliberately concentrating and inhaling
the contents can be harmful or fatal.
.Do not puncture or incinerate. Contents under pressure, Do not store at temperatures above 120°F

Stop Use

·Irritation occurs
·There is no improvement within 4 weeks.

Ask Doctor

·Irritation occurs
·There is no improvement within 4 weeks.

Keep Oot Of Reach Of Children

If swallowed,get medical help or contact a poison control center right away.

Directions

·Wash the affected area and dry thoroughly
·Shake can well and spray a thin layer over
affected area twice daily (morning and night)
·Supervise children in the use of this product
·pay special attention to spaces between
the toes; wear well-fitting, ventilated shoes
and change shoes and socks at least once
daily
·Use daily for 4 weeks; if condition persists
longer, ask a doctor
·To prevent athlete's foot, apply once or
twice daily (morning and/or night, or as
directed by a doctor)
·This product is not effective on the scalp
or nails.

Other information

Store between 20-25°C (68-77°F)

Inactive ingredients

alcohol，benzoic acid，euphorbia hirta whole，phellodendron amurense bark，phenylephrine hydrochloride，pseudolarix amabilis bark，salicylic acid，sophora flavescens root.